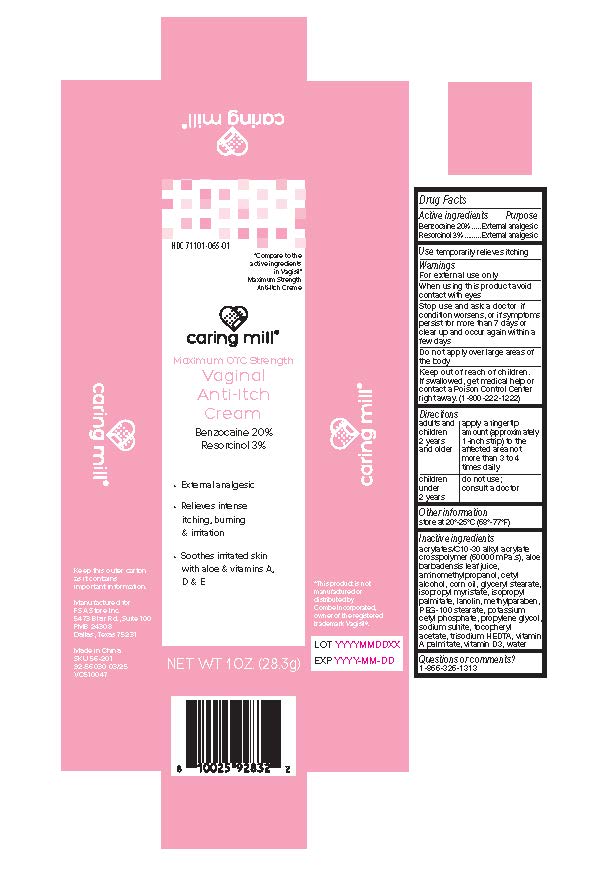 DRUG LABEL: Caring Mills Vaginal Anti-Itch Cream
NDC: 71101-065 | Form: CREAM
Manufacturer: Veridian Healthcare
Category: otc | Type: HUMAN OTC DRUG LABEL
Date: 20251222

ACTIVE INGREDIENTS: BENZOCAINE 20 g/100 g; RESORCINOL 3 g/100 g
INACTIVE INGREDIENTS: PEG-100 MONOSTEARATE; ALOE VERA LEAF; CETYL ALCOHOL; CHOLECALCIFEROL; GLYCERYL MONOSTEARATE; ISOPROPYL MYRISTATE; ISOPROPYL PALMITATE; CORN OIL; PROPYLENE GLYCOL; WATER; VITAMIN A PALMITATE; SODIUM SULFITE; .ALPHA.-TOCOPHEROL ACETATE; TRISODIUM HEDTA; POTASSIUM CETYL PHOSPHATE; LANOLIN; ACRYLATES/C10-30 ALKYL ACRYLATE CROSSPOLYMER (60000 MPA.S); AMINOMETHYL PROPANOL; METHYLPARABEN

Caring Mills Vaginal Anti-Itch Cream

Drug Facts Active ingredients

Benzocaine 20%
Resorcinol 3%

Purpose

External analgesic

Use

temporarily relieves itching

Warnings

For external use only

When using this product

avoid contact with the eyes

Stop use and ask a doctor if

condition worsens, or if symptoms persist for more than7 days or clear up and occur again within a few days

Do not apply

Do not applyover large area of the body.

Other Information

store at 20° -25° C (68° -77° F)

Keep out of reach of children

If swallowed, get medical help or contact a Poison Control Center right away. (1-800-222-1222)

Directions

adults and children 2 years and older | apply a fingertip amount (approximately 1-inch strip) to the affected area not more than 3 to 4 times daily
children under 2 years | do not use; consult a doctor

Inactive Ingredients

aloe vera leaf, alpha tocopherol,butylated hydroxytoluene,carbomer, cetyl alcoholcholecalciferol, glycerylmonostearate, isopropyl myristate,

isopropyl palmitate, isopropyl stearate, mineral oil, PEG 100 stearate, PEG 400, phenoxy ethanol, propylene glycol, sodium hydroxide,
sodium lauryl sulfate, trisodium edta, vitamin a palmitate, water

Questions or comments?

1-866-326-1313